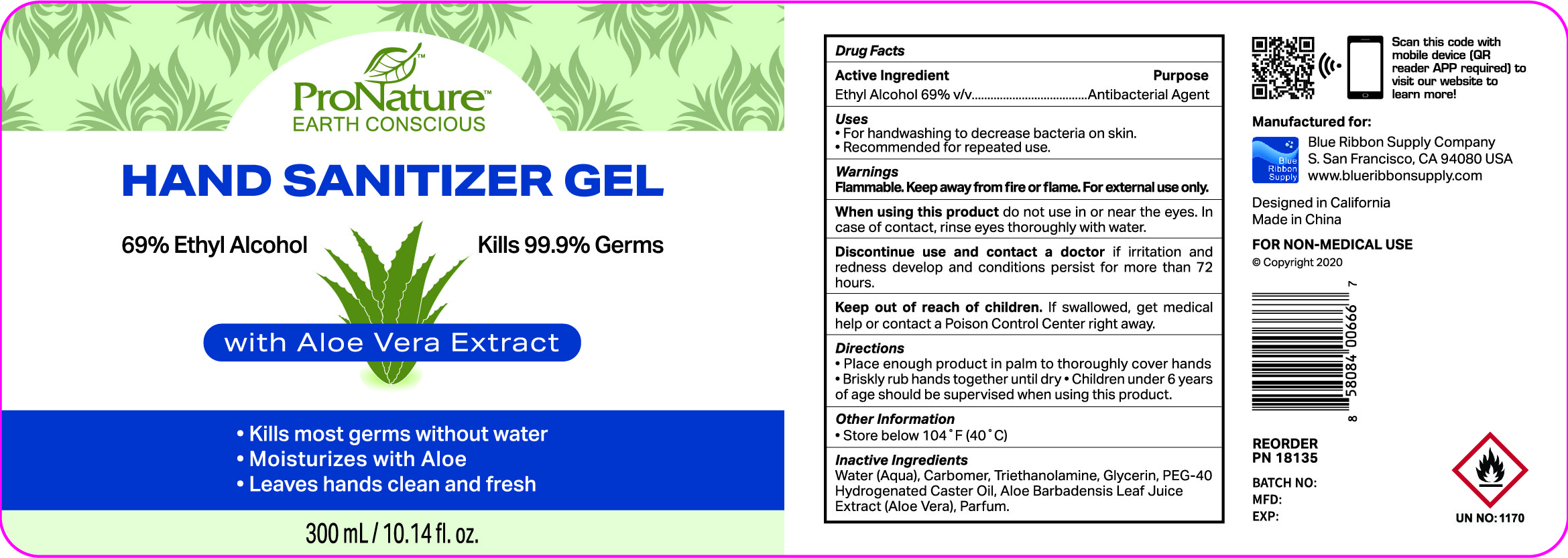 DRUG LABEL: ProNature EARTH CONSCIOUS HAND SANITIZER with Aloe Vera Extract
NDC: 73027-207 | Form: GEL
Manufacturer: JIANGSU HANHE DAILY CHEMICALS CO., LTD.
Category: otc | Type: HUMAN OTC DRUG LABEL
Date: 20211102

ACTIVE INGREDIENTS: ALCOHOL 69 mL/100 mL
INACTIVE INGREDIENTS: CARBOMER 934; TROLAMINE; GLYCERIN; WATER; ALOE VERA LEAF

ACTIVE INGREDIENT

Ethyl Alcohol 69% v/v

Purpose

Antibacterial Agent

Use

For hand washing to decrease bacteria on the skin

Recommended for repeated use

Warnings

For external use only.

Non Medical. Flammable. Keep away from fire or flame

When using this product, do not use in or near eyes, In case of contact, rinse eyes thoroughly with water

STOP USE

Discontinue use and contact a doctor if irritation and redness develop and condition persists for more than 72 hours

Keep out of reach of children. If swallowed, get medical help or contact a poison control center right away

Directions

- Place enough product in palm to thoroughly cover hands
- Briskly rub hands together until dry
- Children under 6 years of age should be supervised when using this product

Other Information

Store below 104F (40C)

Inactive ingredients

Water, Carbomer, Triethanolamine, Glycerin, PEG-40 Hydrogenated Caster Oil, Aloe Barbadensis (Aloe Vera) Leaf Extract, Parfum